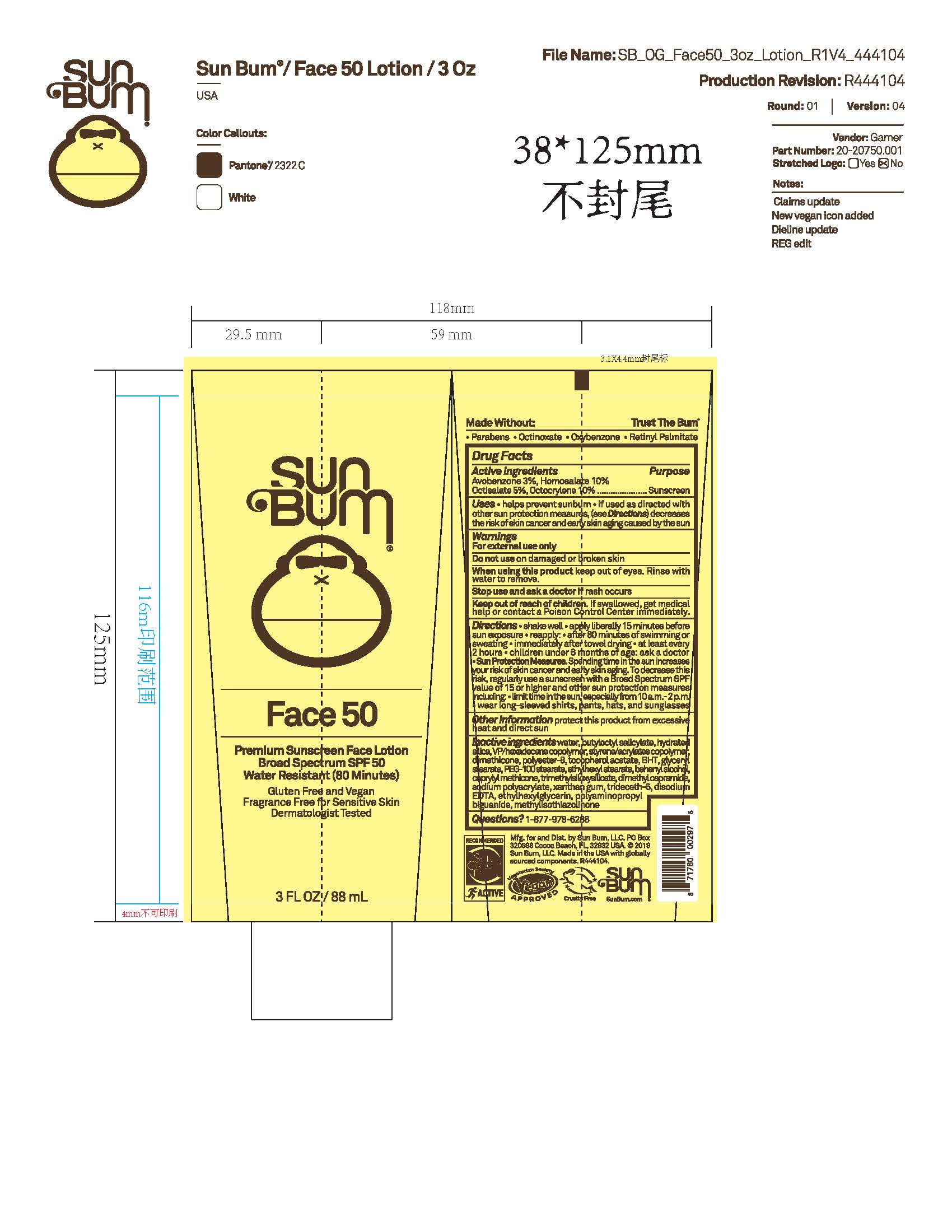 DRUG LABEL: Sun Bum Face 50 Premium Sunscreen
NDC: 69039-782 | Form: LOTION
Manufacturer: Sun Bum, LLC
Category: otc | Type: HUMAN OTC DRUG LABEL
Date: 20250826

ACTIVE INGREDIENTS: AVOBENZONE 30 mg/1 mL; HOMOSALATE 100 mg/1 mL; OCTISALATE 50 mg/1 mL; OCTOCRYLENE 100 mg/1 mL
INACTIVE INGREDIENTS: CAPRYLYL METHICONE; VP/HEXADECENE COPOLYMER; LUVISET 360; PEG-100 STEARATE; ETHYLHEXYLGLYCERIN; BEHENYL ALCOHOL; BUTYLOCTYL SALICYLATE; BHT; TRIDECETH-6; METHYLISOTHIAZOLINONE; GLYCERYL STEARATE; ETHYLHEXYL STEARATE; DIMETHICONE; POLYESTER-8 (1400 MW, CYANODIPHENYLPROPENOYL CAPPED); .ALPHA.-TOCOPHEROL ACETATE; POLYAMINOPROPYL BIGUANIDE; XANTHAN GUM; EDETATE DISODIUM; SODIUM POLYACRYLATE (8000 MW); WATER; TRIMETHYLSILOXYSILICATE (M/Q 0.6-0.8); DIMETHYL CAPRAMIDE; HYDRATED SILICA

Sun Bum Face 50 Premium Sunscreen

Active Ingredients

Avobenzone 3%, Homosalate 10%, Octisalate 5%, Octocrylene 10%

Purpose

Sunscreen

Uses

• helps prevent sunburn • if used as directed with other sun protection measures, (see Directions) decreases the risk of skin cancer and early skin aging caused by the sun

Warnings

For external use only

Do not use on damaged or broken skin

When using this product keep out of eyes. Rinse with water to remove.

Stop use and ask a doctor if rash occurs

Keep out of reach of children. If swallowed, get medical help or contact a Poison Control Center immediately.

Warnings

Keep Out Of Reach Of Children

Directions

• shake well before use

• apply liberally 15 minutes before sun exposure

• reapply: • after 80 minutes of swimming or sweating • immediately after towel drying • at least every 2 hours

• children under 6 months of age: ask a doctor

• Sun Protection Measures. Spending time in the sun increases your risk of skin cancer and early skin aging. To decrease this risk, regularly use a sunscreen with a Broad Spectrum SPF value of 15 or higher and other sun protection measures including:

• limit time in the sun, especially from 10 a.m.- 2 p.m.

• wear long-sleeved shirts, pants, hats and sunglasses

Directions

• shake well before use

• apply liberally 15 minutes before sun exposure

Other Information

protect this product from excessive heat and direct sun

Inactive Ingredients

water, butyloctyl salicylate, hydrated silica, VP/hexadecene copolymer, styrene/acrylates copolymer, dimethicone, polyester-8, tocopherol acetate, BHT, glyceryl stearate, PEG-100 stearate, ethylhexyl stearate, behenyl alcohol, caprylyl methicone, trimethylsiloxysilicate, dimethyl capramide, sodium polyacrylate, xanthan gum, trideceth-6, disodium EDTA, ethylhexylglycerin, polyaminopropyl biguanide, methylisothiazolinone

Questions?

1-877-978-6286